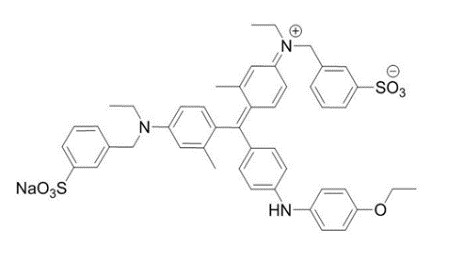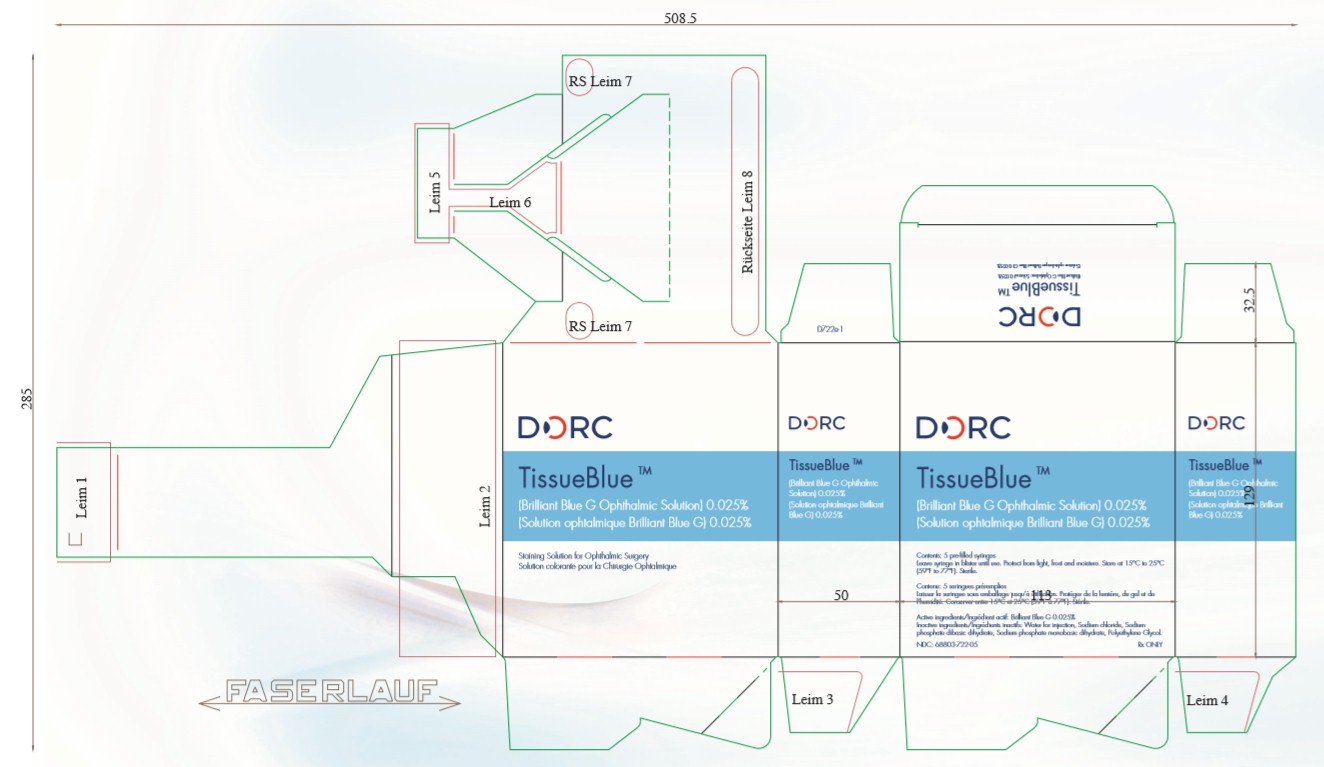 DRUG LABEL: TISSUEBLUE
NDC: 68803-722 | Form: INJECTION, SOLUTION
Manufacturer: D.O.R.C. Dutch Ophthalmic Research Center (International) B.V.
Category: prescription | Type: HUMAN PRESCRIPTION DRUG LABEL
Date: 20250507

ACTIVE INGREDIENTS: BRILLIANT BLUE G 0.0125 mg/0.5 mL
INACTIVE INGREDIENTS: SODIUM CHLORIDE 8.2 mg/0.5 mL; SODIUM PHOSPHATE, DIBASIC, DODECAHYDRATE 3.1 mg/0.5 mL; SODIUM PHOSPHATE, MONOBASIC, DIHYDRATE 0.3 mg/0.5 mL; WATER 4743 g/0.5 mL; POLYETHYLENE GLYCOL 3350 2 mg/0.5 mL

HIGHLIGHTS OF PRESCRIBING INFORMATION

TissueBlue: These highlights do not include all the information needed to use TISSUEBLUE 0.025% safely and effectively. See full prescribing information for TISSUEBLUE 0.025%.
TISSUEBLUE (Brilliant Blue G Ophthalmic Solution) 0.025%, for intraocular ophthalmic use
Initial U.S. Approval: 2019

TissueBlue 0.025% - Indications & Usage Section

TissueBlue 0.025% is a disclosing agent indicated to selectively stain the internal limiting membrane (ILM).

TissueBlue 0.025% - Dosage & Administration Section

- Inject TissueBlue 0.025% directly in a Balanced Salt Solution (BSS)-filled vitreous cavity.
- Excess TissueBlue should be removed from the vitreous cavity.

TissueBlue 0.025% - Dosage forms & Strengths section

TissueBlue (Brilliant Blue G Ophthalmic Solution) 0.025% is supplied in 2.25 mL syringes filled to a volume of 0.5 mL.

TissueBlue 0.025% - Contraindications section

None

TissueBlue 0.025% - Warnings and Precautions section

Excessive staining: Excess TissueBlue 0.025% should be removed from the eye immediately after staining.
Use of the syringe: Make sure the plunger moves smoothly before injecting the solution.

TissueBlue 0.025% - Adverse Reactions section

Adverse reactions that have been reported in procedures that included the use of TissueBlue 0.025% have often been associated with the surgical procedure. The complications include retinal (retinal break, tear, hemorrhage, and detachment and cataracts.

To report SUSPECTED ADVERSE REACTIONS, contact Dutch Ophthalmic, USA at 1-800-75-DUTCH or FDA at
1-800-FDA-1088 or www.fda.gov/medwatch

FULL PRESCRIBING INFORMATION

TissueBlue 0.025% - Indications & Usage Section

TissueBlue 0.025% is indicated to selectively stain the internal limiting membrane (ILM).

TissueBlue 0.025% - Dosage & Administration Section

TissueBlue 0.025% is carefully injected into the Balanced Salt Solution (BSS)-filled vitreous cavity using a blunt cannula attached to the pre-filled syringe, without allowing the cannula to contact the retina or allowing TissueBlue to get under the retina. Sufficient staining is expected within a few seconds. Following staining, all excess dye should be removed from the vitreous cavity.

TissueBlue 0.025% - Dosage forms & Strengths section

TissueBlue (Brilliant Blue G Ophthalmic Solution) 0.025% is a clear, bright blue, single-dose ophthalmic solution supplied in 2.25 mL syringes pre-filled to a volume of 0.5 mL.

TissueBlue 0.025% - Contraindications section

None

TissueBlue 0.025% - Warnings and Precautions section

Excessive Staining
Excess TissueBlue 0.025% should be removed from the eye immediately after staining.

Use of the Syringe
Make sure the plunger moves smoothly before injecting the solution. Do not use the product if the plunger does not move smoothly to prime the cannula.

TissueBlue 0.025% - Adverse Reactions section

Adverse reactions that have been reported in procedures that included the use of Brilliant Blue G Ophthalmic Solution have often been associated with the surgical procedure. These complications include retinal (retinal break, tear, hemorrhage, and detachment) and cataracts.

TissueBlue 0.025% - Use in specific populations section

TissueBlue 0.025% - Pregnancy section

Risk Summary
There are no available data on the use of TissueBlue 0.025% in pregnant women to inform a drug associated risk. Systemic absorption of TissueBlue 0.025% in humans is expected to be negligible following intravitreal injection and subsequent removal of the drug at the completion of surgical procedures. Due to the negligible systemic exposure, it is not expected that maternal use of TissueBlue 0.025% will result in fetal exposure to the drug.

Adequate animal reproduction studies were not conducted with TissueBlue 0.025%.

TissueBlue 0.025% - Lactation section

Risk Summary
No data are available regarding the presence of Brilliant Blue G in human milk after intraocular administration of TissueBlue 0.025%, or the effects on the breastfed infant or the effects on milk production. However, breastfeeding is not expected to result in exposure of the child to Brilliant Blue G due to the expected negligible systemic exposure of BBG in humans following intravitreal injection and subsequent removal of the drug at the completion of surgical procedures.

TissueBlue 0.025% - Pediatric use section

The safety and effectiveness of TissueBlue 0.025% in pediatric patients has not been established.

TissueBlue 0.025% - Geriatric use section

No overall differences in safety or effectiveness were observed between elderly and younger adult patients.

TissueBlue 0.025% - Description section

TissueBlue (Brilliant Blue G Ophthalmic Solution) 0.025% is a sterile solution of BBG (a dye) for intraocular ophthalmic use. Each mL of TissueBlue 0.025% contains BBG 0.25 mg, polyethylene glycol and buffered sodium chloride solution (sodium chloride, dibasic sodium phosphate, monobasic sodium phospage, water for injection). Phosphoric acid and/or sodium hydroxide may also be used for pH adjustment. The pH range of TissueBlue 0.025% Solution is between 7.3 and 7.6.

The drug substance BBG has the chemical name Brilliant Blue G, a molecular weight of 854.02 and has the following chemical structure:

Molecular formula: C47H48N3NaO7S2

TissueBlue 0.025% - Clinical Pharmacology section

TissueBlue 0.025% - Mechanism of action section

Brilliant Blue G has been shown to selectively stain the ILM, but not the epiretinal membrane nor the retina, making it easier to visualize the membrane for removal, although the exact mechanism of this selectivity has not been elucidated.

TissueBlue 0.025% - Nonclinical toxicology section

TissueBlue 0.025% - Nonclinical toxicology section

Studies to evaluate the potential for carcinogenicity or impairment of fertility of TissueBlue 0.025% have not been conducted.
Brilliant Blue G was not mutagenic in the Ames assay, the in vitro mouse lymphoma assay, or the in vivo rat micronucleus assay.

TissueBlue 0.025% - How supplied section

TissueBlue (Brilliant Blue G Ophthalmic Solution), 0.025% is supplied as 0.5 mL of Brilliant Blue G Ophthalmic Solution, 0.025% in a sterile, single-dose Luer Lok, 2.25 mL glass syringe, with a grey rubber plunger stopper and tip cap with polypropylene plunger rod in a pre-formed polypropylene blister pouch sealed with a Tyvek® lid.

NDC 68803-722-05 (One 0.5 mL syringe)
NDC 68803-722-25 (Carton of five 0.5 mL syringes)

TissueBlue 0.025% - Storage and Handling section

TissueBlue 0.025% should be stored at 15°C to 25°C (59°F to 77°F). Protect from light, frost and moisture.

Distributed by:
Dutch Ophthalmic, USA
10 Continental Drive, Bldg 1
Exeter, NH 03833, USA
Phone: 800-75-DUTCH or 603-778-6929

Made in Germany

All trademarks are the property of their respective owners.

Package Label - 0.5 mL

TissueBlue

(Brilliant Blue G Ophthalmic Solution) 0.025%

Staining Solution for Ophthalmic Surgery

Protect from light, frost and moisture. Store at 15°C to 25°C (59°F to 77°F). Sterile.

Active ingredients: Brilliant Blue G 0.025% Inactive ingredients: Water for injection, Sodium chloride, dibasic sodium phosphate, monobasic sodium phosphate, polyethylene glycol, phosphoric acid and/or sodium hydroxide may also be used for pH adjustment.

NDC 68803-722-05 (One 0.5 mL syringe)
NDC 68803-722-25 (Carton of five 0.5 mL syringes)